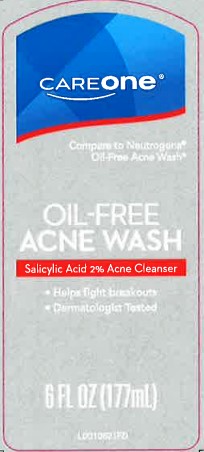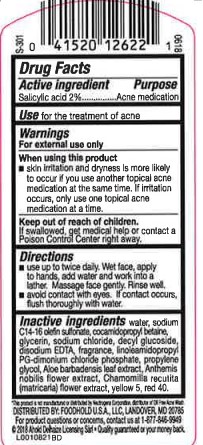 DRUG LABEL: Oil Free Acne Wash
NDC: 41520-948 | Form: LOTION
Manufacturer: American Sales Company
Category: otc | Type: HUMAN OTC DRUG LABEL
Date: 20260206

ACTIVE INGREDIENTS: SALICYLIC ACID 20 mg/1 mL
INACTIVE INGREDIENTS: SODIUM C14-16 OLEFIN SULFONATE; COCAMIDOPROPYL BETAINE; GLYCERIN; SODIUM CHLORIDE; DECYL GLUCOSIDE; EDETATE DISODIUM ANHYDROUS; LINOLEAMIDOPROPYL PG-DIMONIUM CHLORIDE PHOSPHATE; PROPYLENE GLYCOL; ALOE VERA LEAF; CHAMAEMELUM NOBILE FLOWER; CHAMOMILE; FD&C YELLOW NO. 5; FD&C RED NO. 40; WATER

Care One 947.003/947AC-AD
Oil Free Acne Wash

Active ingredient

Salicylic acid 2%

Purpose

Acne medication

Use

for the treatment of acne

Warnings

For external use only

When using this product

- skin irritation and dryness is more likely to occur if you use another topical acne medication at the same time. If irritation occurs, only use one topical acne medication at a time.

Keep out of reach of children.

If swallowed, get medical help or contact a Poison Control Center right away.

Directions

- use up to twice a daily. Wet face, apply to hands, add water and work into lather. Massage face gently. Rinse well.
- avoid contact with eyes. If contact occurs, flush thoroughly with water.

Inactive ingredients

water, sodium C14-16 olefin sulfonate, cocamidopropyl betaine, glycerin, sodium chloride, decyl glucoside, disodium EDTA, fragrance, linoleamidopropyl PG-dimonium chloride phosphate, propylene glycol, Aloe barbadensis leaf extract, Anthemis nobilis flower extract, Chamomilla recutita (matricaria) flower extract, yellow 5, red 40

ADVERSE REACTION

*This product is not manufactured or distributed by NEUTROGENA CORPORATION, distributor of Neutrogena Oil-Free Acne Wash.

Distributed by Foodhold USA, LLC

Landover, MD 20785

For product questions or concerns, contact us at 1-877-848-9949

(c)2018 Ahold Delhaze Licensing S&S Quality guaranteed or your money back

Principal display panel

Care one

Compare to Neutrogena Oil-Free Acne Wash*

Oil-Free Acne Wash

SALICYLIC ACID 2% ACNE Cleanser

- Helps fight breakouts
- Dermatologist tested

6 FL OZ (177 mL)